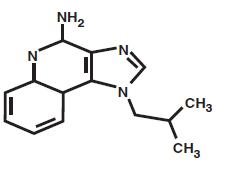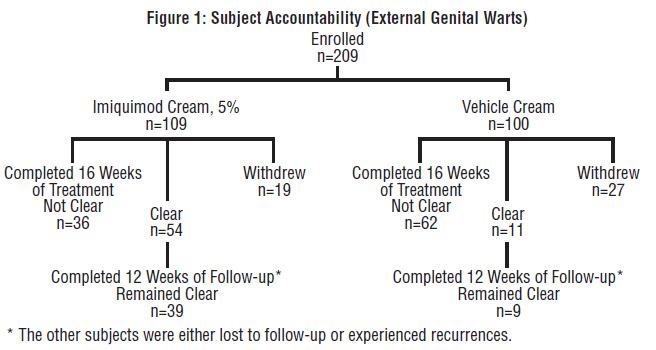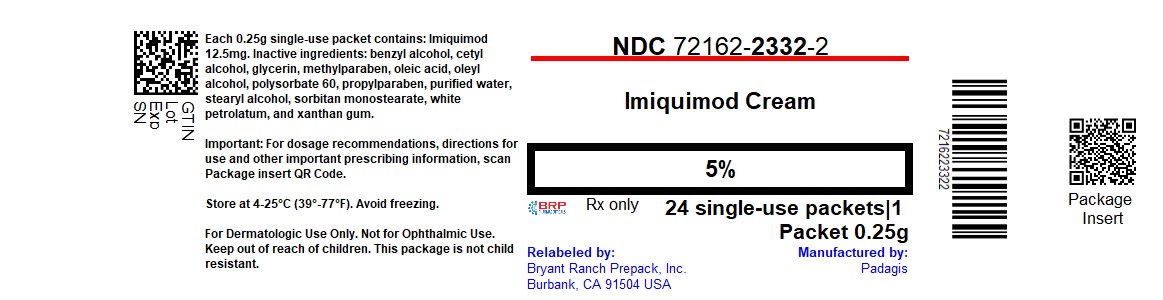 DRUG LABEL: Imiquimod
NDC: 72162-2332 | Form: CREAM
Manufacturer: Bryant Ranch Prepack
Category: prescription | Type: HUMAN PRESCRIPTION DRUG LABEL
Date: 20250925

ACTIVE INGREDIENTS: IMIQUIMOD 12.5 mg/0.25 g
INACTIVE INGREDIENTS: BENZYL ALCOHOL; CETYL ALCOHOL; GLYCERIN; METHYLPARABEN; OLEIC ACID; OLEYL ALCOHOL; POLYSORBATE 60; PROPYLPARABEN; WATER; STEARYL ALCOHOL; SORBITAN MONOSTEARATE; PETROLATUM; XANTHAN GUM

HIGHLIGHTS OF PRESCRIBING INFORMATION

These highlights do not include all the information needed to use Imiquimod Cream safely and effectively. See full prescribing information for Imiquimod Cream.
Imiquimod Cream, 5%
For topical use only
Initial U.S. Approval: 1997

1 INDICATIONS AND USAGE

Imiquimod Cream is indicated for the topical treatment of:

• Clinically typical, nonhyperkeratotic, nonhypertrophic actinic keratoses (AK) on the face or scalp in immunocompetent adults (1.1)

• Biopsy-confirmed, primary superficial basal cell carcinoma (sBCC) in immunocompetent adults; maximum tumor diameter of 2.0 cm on trunk, neck, or extremities (excluding hands and feet), only when surgical methods are medically less appropriate and patient follow-up can be reasonably assured (1.2)

• External genital and perianal warts/condyloma acuminata in patients 12 years old or older (1.3)

Limitations of Use: Efficacy was not demonstrated for molluscum contagiosum in children aged 2-12 (1.4, 8.4)

2 DOSAGE AND ADMINISTRATION

Imiquimod Cream is not for oral, ophthalmic, or intravaginal use (2)

• Actinic keratosis: 2 times per week for a full 16 weeks (2.1)

• Superficial basal cell carcinoma: 5 times per week for a full 6 weeks (2.2)

• External genital warts (EGW): 3 times per week until total clearance or a maximum of 16 weeks (2.3)

3 DOSAGE FORMS AND STRENGTHS

• Imiquimod Cream, 5%, is supplied in single-use packets (12 or 24 per box), each of which contains 250 mg of the cream, equivalent to 12.5 mg of imiquimod. (3)

4 CONTRAINDICATIONS

- None (4)

5 WARNINGS AND PRECAUTIONS

• Intense local inflammatory reactions can occur (e.g., skin weeping, erosion). Dosing interruption may be required (2, 5.1, 6)

• Severe local inflammatory reactions of the female external genitalia can lead to severe vulvar swelling. Severe vulvar swelling can lead to urinary retention; dosing should be interrupted or discontinued.

• Flu-like systemic signs and symptoms including malaise, fever, nausea, myalgias and rigors may occur. Dosing interruption may be required (2, 5.2, 6)

• Avoid exposure to sunlight and sunlamps. Wear sunscreen daily (5.3)

• Safety and efficacy have not been established for repeat courses of treatment to the same area for AK (5.4)

• Imiquimod Cream is not recommended for treatment of BCC subtypes other than the superficial variant, i.e., sBCC (5.5)

• Treatment of urethral, intra-vaginal, cervical, rectal or intra-anal viral disease is not recommended (5.6)

• Safety and efficacy in immunosuppressed patients have not been established (1.5)

6 ADVERSE REACTIONS

Most common adverse reactions (incidence >28%) are application site reactions or local skin reactions: itching, burning, erythema, flaking/scaling/dryness, scabbing/crusting, edema, induration, excoriation, erosion, ulceration. Other reported reactions (1%) include fatigue, fever, and headache (6.1, 6.2, 6.3)

To report SUSPECTED ADVERSE REACTIONS, contact Padagis at 1-866-634-9120 or FDA at 1-800-FDA-1088 or www.fda.gov/medwatch.

FULL PRESCRIBING INFORMATION

1 INDICATIONS AND USAGE

1.1 Actinic Keratosis

Imiquimod Cream is indicated for the topical treatment of clinically typical, nonhyperkeratotic, nonhypertrophic actinic keratoses on the face or scalp in immunocompetent adults.

1.2 Superficial Basal Cell Carcinoma

Imiquimod Cream is indicated for the topical treatment of biopsy-confirmed, primary superficial basal cell carcinoma (sBCC) in immunocompetent adults, with a maximum tumor diameter of 2.0 cm, located on the trunk (excluding anogenital skin), neck, or extremities (excluding hands and feet), only when surgical methods are medically less appropriate and patient follow-up can be reasonably assured.

The histological diagnosis of superficial basal cell carcinoma should be established prior to treatment, since safety and efficacy of Imiquimod Cream have not been established for other types of basal cell carcinomas, including nodular and morpheaform (fibrosing or sclerosing) types.

1.3 External Genital Warts

Imiquimod Cream is indicated for the treatment of external genital and perianal warts/condyloma acuminata in patients 12 years old and older.

1.4 Limitations of Use

Imiquimod cream has been evaluated in children ages 2 to 12 years with molluscum contagiosum and these studies failed to demonstrate efficacy. [see Use in Specific Populations (8.4)].

1.5 Unevaluated Populations

The safety and efficacy of Imiquimod Cream in immunosuppressed patients have not been established.

Imiquimod Cream should be used with caution in patients with pre-existing autoimmune conditions.

The efficacy and safety of Imiquimod Cream have not been established for patients with Basal Cell Nevus Syndrome or Xeroderma Pigmentosum.

2 DOSAGE AND ADMINISTRATION

The application frequency for Imiquimod Cream is different for each indication. Imiquimod Cream is not for oral, ophthalmic, or intravaginal use.

2.1 Actinic Keratosis

Imiquimod Cream should be applied 2 times per week for a full 16 weeks to a defined treatment area on the face or scalp (but not both concurrently). The treatment area is defined as one contiguous area of approximately 25 cm^2 (e.g., 5 cm x 5 cm) on the face (e.g. forehead or one cheek) or on the scalp. Examples of 2 times per week application schedules are Monday and Thursday, or Tuesday and Friday. Imiquimod Cream should be applied to the entire treatment area and rubbed in until the cream is no longer visible. No more than one packet of Imiquimod Cream should be applied to the contiguous treatment area at each application. Imiquimod Cream should be applied prior to normal sleeping hours and left on the skin for approximately 8 hours, after which time the cream should be removed by washing the area with mild soap and water. The prescriber should demonstrate the proper application technique to maximize the benefit of Imiquimod Cream therapy.

It is recommended that patients wash their hands before and after applying Imiquimod Cream. Before applying the cream, the patient should wash the treatment area with mild soap and water and allow the area to dry thoroughly (at least 10 minutes).

Contact with the eyes, lips and nostrils should be avoided.

Local skin reactions in the treatment area are common. [see Adverse Reactions (6.1, 6.5)] A rest period of several days may be taken if required by the patient's discomfort or severity of the local skin reaction. However, the treatment period should not be extended beyond 16 weeks due to missed doses or rest periods. Response to treatment cannot be adequately assessed until resolution of local skin reactions. Lesions that do not respond to treatment should be carefully re-evaluated and management reconsidered.

Imiquimod Cream is packaged in single-use packets, with 12 or 24 packets supplied per box. Patients should be prescribed no more than 36 packets for the 16-week treatment period. Unused packets should be discarded. Partially-used packets should be discarded and not reused.

2.2 Superficial Basal Cell Carcinoma

Imiquimod Cream should be applied 5 times per week for a full 6 weeks to a biopsy-confirmed superficial basal cell carcinoma. An example of a 5 times per week application schedule is to apply Imiquimod Cream, once per day, Monday through Friday. Imiquimod Cream should be applied prior to normal sleeping hours and left on the skin for approximately 8 hours, after which time the cream should be removed by washing the area with mild soap and water. The prescriber should demonstrate the proper application technique to maximize the benefit of Imiquimod Cream therapy.

It is recommended that patients wash their hands before and after applying Imiquimod Cream. The patient should wash the treatment area with mild soap and water before applying the cream, and allow the area to dry thoroughly.

The target tumor should have a maximum diameter of 2 cm and be located on the trunk (excluding anogenital skin), neck, or extremities (excluding hands and feet). The treatment area should include a 1 cm margin of skin around the tumor. Sufficient cream should be applied to cover the treatment area, including 1 centimeter of skin surrounding the tumor. Imiquimod Cream should be rubbed into the treatment area until the cream is no longer visible.

TABLE 1. Amount of Imiquimod Cream to Use for sBCC

Target Tumor; Diameter | Size of Cream Droplet to be Used; (diameter) | Approximate Amount of Imiquimod to be Used
0.5 to < 1.0 cm | 4 mm | 10 mg
≥1.0 to < 1.5 cm | 5 mm | 25 mg
≥1.5 to 2.0 cm | 7 mm | 40 mg

Contact with the eyes, lips and nostrils should be avoided.

Local skin reactions in the treatment area are common. [see Adverse Reactions (6.2, 6.5)] A rest period of several days may be taken if required by the patient's discomfort or severity of the local skin reaction.

Early clinical clearance cannot be adequately assessed until resolution of local skin reactions (e.g. 12 weeks post-treatment). Local skin reactions or other findings (e.g. infection) may require that a patient be seen sooner than the post-treatment assessment for clinical clearance. If there is clinical evidence of persistent tumor at the post-treatment assessment for clinical clearance, a biopsy or other alternative intervention should be considered. Lesions that do not respond to therapy should be carefully re-evaluated and management reconsidered; the safety and efficacy of a repeat course of Imiquimod Cream treatment have not been established. If any suspicious lesion arises in the treatment area at any time after determination of clinical clearance, the patient should seek a medical evaluation. [see Clinical Studies (14.2)].

Imiquimod Cream is packaged in single-use packets, with 12 or 24 packets supplied per box. Patients should be prescribed no more than 36 packets for the 6-week treatment period. Unused packets should be discarded. Partially-used packets should be discarded and not reused.

2.3 External Genital Warts

Imiquimod Cream should be applied 3 times per week to external genital/perianal warts. Imiquimod Cream treatment should continue until there is total clearance of the genital/perianal warts or for a maximum of 16 weeks. Examples of 3 times per week application schedules are: Monday, Wednesday, Friday or Tuesday, Thursday, Saturday. Imiquimod Cream should be applied prior to normal sleeping hours and left on the skin for 6 -10 hours, after which time the cream should be removed by washing the area with mild soap and water. The prescriber should demonstrate the proper application technique to maximize the benefit of Imiquimod Cream therapy.

It is recommended that patients wash their hands before and after applying Imiquimod Cream.

A thin layer of Imiquimod Cream should be applied to the wart area and rubbed in until the cream is no longer visible. The application site should not be occluded. Following the treatment period the cream should be removed by washing the treated area with mild soap and water.

Local skin reactions at the treatment site are common. [see Adverse Reactions (6.3, 6.5)]. A rest period of several days may be taken if required by the patient's discomfort or severity of the local skin reaction. Treatment may resume once the reaction subsides. Non-occlusive dressings such as cotton gauze or cotton underwear may be used in the management of skin reactions.

Imiquimod Cream is packaged in single-use packets which contain sufficient cream to cover a wart area of up to 20 cm^2; use of excessive amounts of cream should be avoided.

3 DOSAGE FORMS AND STRENGTHS

Imiquimod Cream, 5%, is supplied in single-use packets each of which contains 250 mg of the cream, equivalent to 12.5 mg of imiquimod. Imiquimod Cream is supplied in boxes of 12 or 24 packets each.

4 CONTRAINDICATIONS

None.

5 WARNINGS AND PRECAUTIONS

5.1 Local Inflammatory Reactions

Intense local inflammatory reactions including skin weeping or erosion can occur after a few applications of Imiquimod Cream and may require an interruption of dosing. [see Dosage and Administration (2) and Adverse Reactions (6)]. Imiquimod Cream has the potential to exacerbate inflammatory conditions of the skin, including chronic graft versus host disease.

Severe local inflammatory reactions of the female external genitalia can lead to severe vulvar swelling. Severe vulvar swelling can lead to urinary retention. Dosing should be interrupted or discontinued for severe vulvar swelling.

Administration of Imiquimod Cream is not recommended until the skin is completely healed from any previous drug or surgical treatment.

5.2 Systemic Reactions

Flu-like signs and symptoms may accompany, or even precede, local inflammatory reactions and may include malaise, fever, nausea, myalgias and rigors. An interruption of dosing should be considered. [see Adverse Reactions (6)]

5.3 Ultraviolet Light Exposure

Exposure to sunlight (including sunlamps) should be avoided or minimized during use of Imiquimod Cream because of concern for heightened sunburn susceptibility. Patients should be warned to use protective clothing (e.g., a hat) when using Imiquimod Cream. Patients with sunburn should be advised not to use Imiquimod Cream until fully recovered. Patients who may have considerable sun exposure, e.g. due to their occupation, and those patients with inherent sensitivity to sunlight should exercise caution when using Imiquimod Cream.

Imiquimod Cream shortened the time to skin tumor formation in an animal photo-cocarcinogenecity study [see Nonclinical Toxicology (13.1)]. The enhancement of ultraviolet carcinogenicity is not necessarily dependent on phototoxic mechanisms. Therefore, patients should minimize or avoid natural or artificial sunlight exposure.

5.4 Unevaluated Uses: Actinic Keratosis

Safety and efficacy have not been established for Imiquimod Cream in the treatment of actinic keratosis with repeated use, i.e. more than one treatment course, in the same area.

The safety of Imiquimod Cream applied to areas of skin greater than 25 cm^2 (e.g. 5 cm X 5 cm) for the treatment of actinic keratosis has not been established [see Clinical Pharmacology (12.3)].

5.5 Unevaluated Uses: Superficial Basal Cell Carcinoma

The safety and efficacy of Imiquimod Cream have not been established for other types of basal cell carcinomas (BCC), including nodular and morpheaform (fibrosing or sclerosing) types. Imiquimod Cream is not recommended for treatment of BCC subtypes other than the superficial variant (i.e., sBCC). Patients with sBCC treated with Imiquimod Cream should have regular follow-up of the treatment site. [see Clinical Studies (14.2)].

The safety and efficacy of treating sBCC lesions on the face, head and anogenital area have not been established.

5.6 Unevaluated Uses: External Genital Warts

Imiquimod Cream has not been evaluated for the treatment of urethral, intra-vaginal, cervical, rectal, or intra-anal human papilloma viral disease.

6 ADVERSE REACTIONS

Because clinical trials are conducted under widely varying conditions, adverse reaction rates observed in the clinical trials of a drug cannot be directly compared to rates in the clinical trials of another drug and may not reflect the rates observed in practice.

6.1 Clinical Trials Experience: Actinic Keratosis

The data described below reflect exposure to imiquimod cream or vehicle in 436 subjects enrolled in two double-blind, vehicle-controlled studies. Subjects applied imiquimod cream or vehicle to a 25 cm^2 contiguous treatment area on the face or scalp 2 times per week for 16 weeks.

Table 2: Selected Adverse Reactions Occurring in > 1% of Imiquimod-Treated Subjects and at a Greater Frequency than with Vehicle in the Combined Studies (Actinic Keratosis)

Preferred Term | Imiquimod Cream; (n= 215) | Vehicle; (n= 221)
Application Site Reaction | 71 (33%) | 32 (14%)
Upper Resp Tract Infection | 33 (15%) | 27 (12%)
Sinusitis | 16 (7%) | 14 (6%)
Headache | 11 (5%) | 7 (3%)
Carcinoma Squamous | 8 (4%) | 5 (2%)
Diarrhea | 6 (3%) | 2 (1%)
Eczema | 4 (2%) | 3 (1%)
Back Pain | 3 (1%) | 2 (1%)
Fatigue | 3 (1%) | 2 (1%)
Fibrillation Atrial | 3 (1%) | 2 (1%)
Infection Viral | 3 (1%) | 2 (1%)
Dizziness | 3 (1%) | 1 (<1%)
Vomiting | 3 (1%) | 1 (<1%)
Urinary Tract Infection | 3 (1%) | 1 (<1%)
Fever | 3 (1%) | 0 (0%)
Rigors | 3 (1%) | 0 (0%)
Alopecia | 3 (1%) | 0 (0%)

Table 3: Application Site Reactions Reported by > 1% of Imiquimod-Treated Subjects and at a Greater Frequency than with Vehicle in the Combined Studies (Actinic Keratosis)

Included Term | Imiquimod Cream; n=215 | Vehicle; n=221
Itching | 44 (20%) | 17 (8%)
Burning | 13 (6%) | 4 (2%)
Bleeding | 7 (3%) | 1 (<1%)
Stinging | 6 (3%) | 2 (1%)
Pain | 6 (3%) | 2 (1%)
Induration | 5 (2%) | 3 (1%)
Tenderness | 4 (2%) | 3 (1%)
Irritation | 4 (2%) | 0 (0%)

Local skin reactions were collected independently of the adverse reaction "application site reaction" in an effort to provide a better picture of the specific types of local reactions that might be seen. The most frequently reported local skin reactions were erythema, flaking/scaling/dryness, and scabbing/crusting. The prevalence and severity of local skin reactions that occurred during controlled studies are shown in the following table.

Table 4: Local Skin Reactions in the Treatment Area as Assessed by the Investigator (Actinic Keratosis)

 | Imiquimod Cream; (n=215) |  | Vehicle; (n=220)
 | All Grades* | Severe | All Grades* | Severe
Erythema | 209 (97%) | 38 (18%) | 206 (93%) | 5 (2%)
Flaking/Scaling/Dryness | 199 (93%) | 16 (7%) | 199 (91%) | 7 (3%)
Scabbing/Crusting | 169 (79%) | 18 (8%) | 92 (42%) | 4 (2%)
Edema | 106 (49%) | 0 (0%) | 22 (10%) | 0 (0%)
Erosion/Ulceration | 103 (48%) | 5 (2%) | 20 (9%) | 0 (0%)
Weeping/Exudate | 45 (22%) | 0 (0%) | 3 (1%) | 0 (0%)
Vesicles | 19 (9%) | 0 (0%) | 2 (1%) | 0 (0%)
*Mild, Moderate, or Severe

The adverse reactions that most frequently resulted in clinical intervention (e.g., rest periods, withdrawal from study) were local skin and application site reactions. Overall, in the clinical studies, 2% (5/215) of subjects discontinued for local skin/application site reactions. Of the 215 subjects treated, 35 subjects (16%) on imiquimod cream and 3 of 220 subjects (1%) on vehicle cream had at least one rest period. Of these imiquimod cream subjects, 32 (91%) resumed therapy after a rest period.

In the AK studies, 22 of 678 (3.2%) of imiquimod-treated subjects developed treatment site infections that required a rest period off imiquimod cream and were treated with antibiotics (19 with oral and 3 with topical).

Of the 206 imiquimod subjects with both baseline and 8-week post-treatment scarring assessments, 6 (2.9%) had a greater degree of scarring scores at 8-weeks post-treatment than at baseline.

6.2 Clinical Trials Experience: Superficial Basal Cell Carcinoma

The data described below reflect exposure to imiquimod cream or vehicle in 364 subjects enrolled in two double-blind, vehicle-controlled studies. Subjects applied imiquimod cream or vehicle 5 times per week for 6 weeks. The incidence of adverse reactions reported by > 1% of subjects during the studies is summarized below.

Table 5: Selected Adverse Reactions Reported by > 1% of Imiquimod-Treated Subjects and at a Greater Frequency than with Vehicle in the Combined Studies (Superficial Basal Cell Carcinoma)

Preferred Term | Imiquimod Cream; (n= 185); N % | Vehicle; (n= 179); N %
Application Site Reaction | 52 (28%) | 5 (3%)
Headache | 14 (8%) | 4 (2%)
Back Pain | 7 (4%) | 1 (<1%)
Upper Resp Tract Infection | 6 (3%) | 2 (1%)
Rhinitis | 5 (3%) | 1 (<1%)
Lymphadenopathy | 5 (3%) | 1 (<1%)
Fatigue | 4 (2%) | 2 (1%)
Sinusitis | 4 (2%) | 1 (<1%)
Dyspepsia | 3 (2%) | 2 (1%)
Coughing | 3 (2%) | 1 (<1%)
Fever | 3 (2%) | 0 (0%)
Dizziness | 2 (1%) | 1 (<1%)
Anxiety | 2 (1%) | 1 (<1%)
Pharyngitis | 2 (1%) | 1 (<1%)
Chest Pain | 2 (1%) | 0 (0%)
Nausea | 2 (1%) | 0 (0%)

The most frequently reported adverse reactions were local skin and application site reactions including erythema, edema, induration, erosion, flaking/scaling, scabbing/crusting, itching and burning at the application site. The incidence of application site reactions reported by > 1% of the subjects during the 6 week treatment period is summarized in the table below.

Table 6: Application Site Reactions Reported by > 1% of Imiquimod-Treated Subjects and at a Greater Frequency than with Vehicle in the Combined Studies (Superficial Basal Cell Carcinoma)

Included Term | Imiquimod Cream; n=185 | Vehicle; n=179
Itching | 30 (16%) | 1 (1%)
Burning | 11 (6%) | 2 (1%)
Pain | 6 (3%) | 0 (0%)
Bleeding | 4 (2%) | 0 (0%)
Erythema | 3 (2%) | 0 (0%)
Papule(s) | 3 (2%) | 0 (0%)
Tenderness | 2 (1%) | 0 (0%)
Infection | 2 (1%) | 0 (0%)

Local skin reactions were collected independently of the adverse reaction "application site reaction" in an effort to provide a better picture of the specific types of local reactions that might be seen. The prevalence and severity of local skin reactions that occurred during controlled studies are shown in the following table.

Table 7: Local Skin Reactions in the Treatment Area as Assessed by the Investigator (Superficial Basal Cell Carcinoma)

 | Imiquimod Cream; n=184 |  | Vehicle; n=178
 | All Grades* | Severe | All Grades* | Severe
Erythema | 184 (100%) | 57 (31%) | 173 (97%) | 4 (2%)
Flaking/Scaling | 167 (91%) | 7 (4%) | 135 (76%) | 0 (0%)
Induration | 154 (84%) | 11 (6%) | 94 (53%) | 0 (0%)
Scabbing/Crusting | 152 (83%) | 35 (19%) | 61 (34%) | 0 (0%)
Edema | 143 (78%) | 13 (7%) | 64 (36%) | 0 (0%)
Erosion | 122 (66%) | 23 (13%) | 25 (14%) | 0 (0%)
Ulceration | 73 (40%) | 11 (6%) | 6 (3%) | 0 (0%)
Vesicles | 57 (31%) | 3 (2%) | 4 (2%) | 0 (0%)
*Mild, Moderate, or Severe

The adverse reactions that most frequently resulted in clinical intervention (e.g., rest periods, withdrawal from study) were local skin and application site reactions; 10% (19/185) of subjects received rest periods. The average number of doses not received per subject due to rest periods was 7 doses with a range of 2 to 22 doses; 79% of subjects (15/19) resumed therapy after a rest period. Overall, in the clinical studies, 2% (4/185) of subjects discontinued for local skin/application site reactions.

In the sBCC studies, 17 of 1266 (1.3%) imiquimod treated subjects developed treatment site infections that required a rest period and treatment with antibiotics.

6.3 Clinical Trials Experience: External Genital Warts

In controlled clinical trials for genital warts, the most frequently reported adverse reactions were local skin and application site reactions.

Some subjects also reported systemic reactions. Overall, 1.2% (4/327) of the subjects discontinued due to local skin/application site reactions. The incidence and severity of local skin reactions during controlled clinical trials are shown in the following table.

Table 8: Local Skin Reactions in the Treatment Area as Assessed by the Investigator (External Genital Warts)

 | Imiquimod Cream |  |  |  | Vehicle
 | Females; n=114 |  | Males; n=156 |  | Females; n=99 |  | Males; n=157
 | All Grades* | Severe | All Grades* | Severe | All Grades* | Severe | All Grades* | Severe
Erythema | 74(65%) | 4(4%) | 90(58%) | 6(4%) | 21(21%) | 0(0%) | 34(22%) | 0(0%)
Erosion | 35(31%) | 1(1%) | 47(30%) | 2(1%) | 8(8%) | 0(0%) | 10(6%) | 0(0%)
Excoriation/; Flaking | 21(18%) | 0(0%) | 40(26%) | 1(1%) | 8(8%) | 0(0%) | 12(8%) | 0(0%)
Edema | 20(18%) | 1(1%) | 19(12%) | 0(0%) | 5(5%) | 0(0%) | 1(1%) | 0(0%)
Scabbing | 4(4%) | 0(0%) | 20(13%) | 0(0%) | 0(0%) | 0(0%) | 4(3%) | 0(0%)
Induration | 6(5%) | 0(0%) | 11(7%) | 0(0%) | 2(2%) | 0(0%) | 3(2%) | 0(0%)
Ulceration | 9(8%) | 3(3%) | 7(4%) | 0(0%) | 1(1%) | 0(0%) | 1(1%) | 0(0%)
Vesicles | 3(3%) | 0(0%) | 3(2%) | 0(0%) | 0(0%) | 0(0%) | 0(0%) | 0(0%)
*Mild, Moderate, or Severe

Remote site skin reactions were also reported. The severe remote site skin reactions reported for females were erythema (3%), ulceration (2%), and edema (1%); and for males, erosion (2%), and erythema, edema, induration, and excoriation/flaking (each 1%).

Selected adverse reactions judged to be probably or possibly related to imiquimod cream are listed below.

Table 9: Selected Treatment Related Reactions (External Genital Warts)

 | Females |  | Males
 | Imiquimod Cream; n=117 | Vehicle; n=103 | Imiquimod Cream; n=156 | Vehicle; n=158
Application Site Disorders:
Application Site Reactions
Wart Site:
Itching | 38(32%) | 21(20%) | 34(22%) | 16(10%)
Burning | 30(26%) | 12(12%) | 14(9%) | 8(5%)
Pain | 9(8%) | 2(2%) | 3(2%) | 1(1%)
Soreness | 3(3%) | 0(0%) | 0(0%) | 1(1%)
Fungal Infection* | 13(11%) | 3(3%) | 3(2%) | 1(1%)
Systemic Reactions:
Headache | 5(4%) | 3(3%) | 8(5%) | 3(2%)
Influenza-like symptoms | 4(3%) | 2(2%) | 2(1%) | 0(0%)
Myalgia | 1(1%) | 0(0%) | 2(1%) | 1(1%)

*Incidences reported without regard to causality with imiquimod cream.

Adverse reactions judged to be possibly or probably related to imiquimod cream and reported by more than 1% of subjects included:

Application Site Disorders: burning, hypopigmentation, irritation, itching, pain, rash, sensitivity, soreness, stinging, tenderness

Remote Site Reactions: bleeding, burning, itching, pain, tenderness, tinea cruris

Body as a Whole: fatigue, fever, influenza-like symptoms

Central and Peripheral Nervous System Disorders: headache

Gastro-Intestinal System Disorders: diarrhea

Musculo-Skeletal System Disorders: myalgia

6.4 Clinical Trials Experience: Dermal Safety Studies

Provocative repeat insult patch test studies involving induction and challenge phases produced no evidence that imiquimod cream causes photoallergenicity or contact sensitization in healthy skin; however, cumulative irritancy testing revealed the potential for imiquimod cream to cause irritation, and application site reactions were reported in the clinical studies [see Adverse Reactions (6)].

6.5 Postmarketing Experience

The following adverse reactions have been identified during post-approval use of imiquimod cream. Because these reactions are reported voluntarily from a population of uncertain size, it is not always possible to reliably estimate their frequency or establish a causal relationship to drug exposure.

Application Site Disorders: tingling at the application site

Body as a Whole: angioedema

Cardiovascular: capillary leak syndrome, cardiac failure, cardiomyopathy, pulmonary edema, arrhythmias (tachycardia, atrial fibrillation, palpitations), chest pain, ischemia, myocardial infarction, syncope

Endocrine: thyroiditis

Gastro-Intestinal System Disorders: abdominal pain

Hematological: decreases in red cell, white cell and platelet counts (including idiopathic thrombocytopenic purpura), lymphoma

Hepatic: abnormal liver function

Infections and Infestation: herpes simplex

Musculo-Skeletal System Disorders: arthralgia

Neuropsychiatric: agitation, cerebrovascular accident, convulsions (including febrile convulsions), depression, insomnia, multiple sclerosis aggravation, paresis, suicide

Respiratory: dyspnea

Urinary System Disorders: proteinuria, dysuria, urinary retention

Skin and Appendages: exfoliative dermatitis, erythema multiforme, hyperpigmentation, hypertrophic scar

Vascular: Henoch-Schonlein purpura syndrome

8 USE IN SPECIFIC POPULATIONS

8.1 Pregnancy

TERATOGENIC EFFECTS

Pregnancy Category C:

Note: The Maximum Recommended Human Dose (MRHD) was set at 2 packets per treatment of Imiquimod Cream (25 mg imiquimod) for the animal multiple of human exposure ratios presented in this label. If higher doses than 2 packets of imiquimod cream are used clinically, then the animal multiple of human exposure would be reduced for that dose. A non-proportional increase in systemic exposure with increased dose of imiquimod cream was noted in the clinical pharmacokinetic study conducted in actinic keratosis subjects [see Clinical Pharmacology (12.3)]. The AUC after topical application of 6 packets of imiquimod cream was 8 fold greater than the AUC after topical application of 2 packets of imiquimod cream in actinic keratosis subjects. Therefore, if a dose of 6 packets per treatment of imiquimod cream was topically administered to an individual, then the animal multiple of human exposure would be either 1/3 of the value provided in the label (based on body surface area comparisons) or 1/8 of the value provided in the label (based on AUC comparisons). The animal multiples of human exposure calculations were based on weekly dose comparisons for the carcinogenicity studies described in this label. The animal multiples of human exposure calculations were based on daily dose comparisons for the reproductive toxicology studies described in this label.

Systemic embryofetal development studies were conducted in rats and rabbits. Oral doses of 1, 5, and 20 mg/kg/day imiquimod were administered during the period of organogenesis (gestational days 6 – 15) to pregnant female rats. In the presence of maternal toxicity, fetal effects noted at 20 mg/kg/day (577X MRHD based on AUC comparisons) included increased resorptions, decreased fetal body weights, delays in skeletal ossification, bent limb bones, and two fetuses in one litter (2 of 1567 fetuses) demonstrated exencephaly, protruding tongues and low-set ears. No treatment related effects on embryofetal toxicity or teratogenicity were noted at 5 mg/kg/day (98X MRHD based on AUC comparisons).

Intravenous doses of 0.5, 1 and 2 mg/kg/day imiquimod were administered during the period of organogenesis (gestational days 6 – 18) to pregnant female rabbits. No treatment related effects on embryofetal toxicity or teratogenicity were noted at 2 mg/kg/day (1.5X MRHD based on BSA comparisons), the highest dose evaluated in this study, or 1 mg/kg/day (407X MRHD based on AUC comparisons).

A combined fertility and peri- and post-natal development study was conducted in rats. Oral doses of 1, 1.5, 3 and 6 mg/kg/day imiquimod were administered to male rats from 70 days prior to mating through the mating period and to female rats from 14 days prior to mating through parturition and lactation. No effects on growth, fertility, reproduction or post-natal development were noted at doses up to 6 mg/kg/day (87X MRHD based on AUC comparisons), the highest dose evaluated in this study. In the absence of maternal toxicity, bent limb bones were noted in the F1 fetuses at a dose of 6 mg/kg/day (87X MRHD based on AUC comparisons). This fetal effect was also noted in the oral rat embryofetal development study conducted with imiquimod. No treatment related effects on teratogenicity were noted at 3 mg/kg/day (41X MRHD based on AUC comparisons).

There are no adequate and well-controlled studies in pregnant women. Imiquimod Cream should be used during pregnancy only if the potential benefit justifies the potential risk to the fetus.

8.3 Nursing Mothers

It is not known whether imiquimod is excreted in human milk following use of Imiquimod Cream. Because many drugs are excreted in human milk, caution should be exercised when Imiquimod Cream is administered to nursing women.

8.4 Pediatric Use

AK and sBCC are not conditions generally seen within the pediatric population. The safety and efficacy of Imiquimod Cream for AK or sBCC in patients less than 18 years of age have not been established.

Safety and efficacy in patients with external genital/perianal warts below the age of 12 years have not been established.

Imiquimod cream was evaluated in two randomized, vehicle-controlled, double-blind trials involving 702 pediatric subjects with molluscum contagiosum (MC) (470 exposed to imiquimod; median age 5 years, range 2-12 years). Subjects applied imiquimod cream or vehicle 3 times weekly for up to 16 weeks. Complete clearance (no MC lesions) was assessed at Week 18. In Study 1, the complete clearance rate was 24% (52/217) in the imiquimod cream group compared with 26% (28/106) in the vehicle group. In Study 2, the clearance rates were 24% (60/253) in the imiquimod cream group compared with 28% (35/126) in the vehicle group. These studies failed to demonstrate efficacy.

Similar to the studies conducted in adults, the most frequently reported adverse reaction from 2 studies in children with molluscum contagiosum was application site reaction. Adverse events which occurred more frequently in Imiquimod-treated subjects compared with vehicle-treated subjects generally resembled those seen in studies in indications approved for adults and also included otitis media (5% imiquimod vs. 3% vehicle) and conjunctivitis (3% imiquimod vs. 2% vehicle).

Erythema was the most frequently reported local skin reaction. Severe local skin reactions reported by treated subjects in the pediatric studies included erythema (28%), edema (8%), scabbing/crusting (5%), flaking/scaling (5%), erosion (2%) and weeping/exudate (2%).

Systemic absorption of imiquimod across the affected skin of 22 subjects aged 2 to 12 years with extensive MC involving at least 10% of the total body surface area was observed after single and multiple doses at a dosing frequency of 3 applications per week for 4 weeks. The investigator determined the dose applied, either 1, 2 or 3 packets per dose, based on the size of the treatment area and the subject’s weight. The overall median peak serum drug concentrations at the end of week 4 was between 0.26 and 1.06 ng/mL except in a 2-year old female who was administered 2 packets of study drug per dose, had a Cmax of 9.66 ng/mL after multiple dosing. Children aged 2-5 years received doses of 12.5 mg (one packet) or 25 mg (two packets) of imiquimod and had median multiple-dose peak serum drug levels of approximately 0.2 or 0.5 ng/mL, respectively. Children aged 6-12 years received doses of 12.5 mg, 25 mg, or 37.5 mg (three packets) and had median multiple dose serum drug levels of approximately 0.1, 0.15, or 0.3 ng/mL, respectively. Among the 20 subjects with evaluable laboratory assessments, the median WBC count decreased by 1.4 x 10^9/L and the median absolute neutrophil count decreased by 1.42 x 10^9/L.

8.5 Geriatric Use

Of the 215 subjects treated with imiquimod cream in the AK clinical studies, 127 subjects (59%) were 65 years and older, while 60 subjects (28%) were 75 years and older. Of the 185 subjects treated with imiquimod cream in the sBCC clinical studies, 65 subjects (35%) were 65 years and older, while 25 subjects (14%) were 75 years and older. No overall differences in safety or effectiveness were observed between these subjects and younger subjects. No other clinical experience has identified differences in responses between the elderly and younger subjects, but greater sensitivity of some older individuals cannot be ruled out.

10 OVERDOSAGE

Topical overdosing of Imiquimod Cream could result in an increased incidence of severe local skin reactions and may increase the risk for systemic reactions.

The most clinically serious adverse event reported following multiple oral imiquimod doses of >200 mg (equivalent to imiquimod content of >16 packets) was hypotension, which resolved following oral or intravenous fluid administration.

11 DESCRIPTION

Imiquimod Cream, 5% is an immune response modifier for topical administration. Each gram contains 50 mg of imiquimod in an off-white oil-in-water vanishing cream base consisting of benzyl alcohol, cetyl alcohol, glycerin, methylparaben, oleic acid, oleyl alcohol, polysorbate 60, propylparaben, purified water, stearyl alcohol, sorbitan monostearate, white petrolatum, and xanthan gum.

Chemically, imiquimod is 1-(2-methylpropyl)-1H-imidazo[4,5-c]quinolin-4-amine. Imiquimod has a molecular formula of C14H16N4 and a molecular weight of 240.3. Its structural formula is:

12 CLINICAL PHARMACOLOGY

12.1 Mechanism of Action

The mechanism of action of Imiquimod Cream in treating AK and sBCC lesions is unknown.

12.2 Pharmacodynamics

Actinic Keratosis

In a study of 18 subjects with AK comparing imiquimod cream to vehicle, increases from baseline in week 2 biomarker levels were reported for CD3, CD4, CD8, CD11c, and CD68 for imiquimod cream treated subjects; however, the clinical relevance of these findings is unknown.

Superficial Basal Cell Carcinoma

An open label study in six subjects with sBCC suggests that treatment with imiquimod cream may increase the infiltration of lymphocytes, dendritic cells, and macrophages into the tumor lesion; however, the clinical significance of these findings is unknown.

External Genital Warts

Imiquimod has no direct antiviral activity in cell culture. A study in 22 subjects with genital/perianal warts comparing imiquimod cream and vehicle shows that imiquimod cream induces mRNA encoding cytokines including interferon-ɑ at the treatment site. In addition HPVL1 mRNA and HPV DNA are significantly decreased following treatment. However, the clinical relevance of these findings is unknown.

12.3 Pharmacokinetics

Systemic absorption of imiquimod across the affected skin of 58 subjects with AK was observed with a dosing frequency of 3 applications per week for 16 weeks. Mean peak serum drug concentrations at the end of week 16 were approximately 0.1, 0.2, and 3.5 ng/mL for the applications to face (12.5 mg imiquimod, 1 single-use packet), scalp (25 mg, 2 packets) and hands/arms (75 mg, 6 packets), respectively.

Table 10: Mean Serum Imiquimod Concentration in Adults Following
Administration of the Last Topical Dose During Week 16
(Actinic Keratosis)
Amount of Imiquimod Cream applied | Mean peak serum imiquimod; concentration [Cmax]
12.5 mg (1 packet) | 0.1 ng/mL
25 mg (2 packets) | 0.2 ng/mL
75 mg (6 packets) | 3.5 ng/mL

The application surface area was not controlled when more than one packet was used. Dose proportionality was not observed. However it appears that systemic exposure may be more dependent on surface area of application than amount of applied dose. The apparent half-life was approximately 10 times greater with topical dosing than the 2 hour apparent half-life seen following subcutaneous dosing, suggesting prolonged retention of drug in the skin. Mean urinary recoveries of imiquimod and metabolites combined were 0.08 and 0.15% of the applied dose in the group using 75 mg (6 packets) for males and females, respectively following 3 applications per week for 16 weeks.

Systemic absorption of imiquimod was observed across the affected skin of 12 subjects with genital/perianal warts, with an average dose of 4.6 mg. Mean peak drug concentration of approximately 0.4 ng/mL was seen during the study. Mean urinary recoveries of imiquimod and metabolites combined over the whole course of treatment, expressed as percent of the estimated applied dose, were 0.11 and 2.41% in the males and females, respectively.

13 NONCLINICAL TOXICOLOGY

13.1 Carcinogenesis, Mutagenesis, Impairment of Fertility

In an oral (gavage) rat carcinogenicity study, imiquimod was administered to Wistar rats on a 2X/week (up to 6 mg/kg/day) or daily (3 mg/kg/day) dosing schedule for 24 months. No treatment related tumors were noted in the oral rat carcinogenicity study up to the highest doses tested in this study of 6 mg/kg administered 2X/week in female rats (87X MRHD based on weekly AUC comparisons), 4 mg/kg administered 2X/week in male rats (75X MRHD based on weekly AUC comparisons) or 3 mg/kg administered 7X/week to male and female rats (153X MRHD based on weekly AUC comparisons).

In a dermal mouse carcinogenicity study, imiquimod cream (up to 5 mg/kg/application imiquimod or 0.3% imiquimod cream) was applied to the backs of mice 3X/week for 24 months. A statistically significant increase in the incidence of liver adenomas and carcinomas was noted in high dose male mice compared to control male mice (251X MRHD based on weekly AUC comparisons). An increased number of skin papillomas was observed in vehicle cream control group animals at the treated site only. The quantitative composition of the vehicle cream used in the dermal mouse carcinogenicity study is the same as the vehicle cream used for imiquimod cream, minus the active moiety (imiquimod).

In a 52-week dermal photo-cocarcinogenecity study, the median time to onset of skin tumor formation was decreased in hairless mice following chronic topical dosing (3X/week; 40 weeks of treatment followed by 12 weeks of observation) with concurrent exposure to UV radiation (5 days per week) with the imiquimod cream vehicle alone. No additional effect on tumor development beyond the vehicle effect was noted with the addition of the active ingredient, imiquimod, to the vehicle cream.

Imiquimod revealed no evidence of mutagenic or clastogenic potential based on the results of five in vitro genotoxicity tests (Ames assay, mouse lymphoma L5178Y assay, Chinese hamster ovary cell chromosome aberration assay, human lymphocyte chromosome aberration assay and SHE cell transformation assay) and three in vivo genotoxicity tests (rat and hamster bone marrow cytogenetics assay and a mouse dominant lethal test).

Daily oral administration of imiquimod to rats, throughout mating, gestation, parturition and lactation, demonstrated no effects on growth, fertility or reproduction, at doses up to 87X MRHD based on AUC comparisons.

14 CLINICAL STUDIES

14.1 Actinic Keratosis

In two double-blind, vehicle-controlled clinical studies, 436 subjects with AK were randomized to treatment with either imiquimod cream or vehicle cream 2 times per week for 16 weeks. The studies enrolled subjects with 4 to 8 clinically typical, visible, discrete, nonhyperkeratotic, nonhypertrophic AK lesions within a 25 cm^2 contiguous treatment area on either the face or scalp. The 25 cm^2 contiguous treatment area could be of any dimensions e.g., 5 cm x 5 cm, 3 cm by 8.3 cm, 2 cm by 12.5 cm. Study subjects ranged from 37 to 88 years of age (median 66 years) and 55% had Fitzpatrick skin type I or II. All imiquimod-treated subjects were Caucasians.

On a scheduled dosing day, the study cream was applied to the entire treatment area prior to normal sleeping hours and left on for approximately 8 hours. Twice weekly dosing was continued for a total of 16 weeks. The clinical response of each subject was evaluated 8 weeks after the last scheduled application of study cream. Efficacy was assessed by the complete clearance rate, defined as the proportion of subjects at the 8-week post-treatment visit with no (zero) clinically visible AK lesions in the treatment area. Complete clearance included clearance of all baseline lesions, as well as any new or sub-clinical AK lesions which appeared during therapy.

Complete and partial clearance rates are shown in the table below. The partial clearance rate was defined as the percentage of subjects in whom 75% or more baseline AK lesions were cleared.

Table 11: Clearance Rates (AK)
Complete Clearance Rates (100% AK Lesions Cleared)
Study | Imiquimod Cream | Vehicle
Study | 46% (49/107) | 3% (3/110)
AK1
Study | 44% (48/108) | 4% (4/111)
AK2
Partial and Complete Clearance Rates
(75% or More Baseline AK Lesions Cleared)
Study | Imiquimod Cream | Vehicle
Study | 60% (64/107) | 10% (11/110)
AK1
Study | 58% (63/108) | 14% (15/111)
AK2

Sub-clinical AK lesions may become apparent in the treatment area during treatment with imiquimod cream. During the course of treatment, 48% (103/215) of subjects experienced an increase in AK lesions relative to the number present at baseline within the treatment area. Subjects with an increase in AK lesions had a similar response to those with no increase in AK lesions.

14.2 Superficial Basal Cell Carcinoma

In two double-blind, vehicle-controlled clinical studies, 364 subjects with primary sBCC were treated with imiquimod cream or vehicle cream 5 times per week for 6 weeks. Target tumors were biopsy-confirmed sBCC and had a minimum area of 0.5 cm^2 and a maximum diameter of 2.0 cm (4.0 cm^2). Target tumors were not to be located within 1.0 cm of the hairline, or on the anogenital area or on the hands or feet, or to have any atypical features. The population ranged from 31-89 years of age (median 60 years) and 65% had Fitzpatrick skin type I or II. On a scheduled dosing day, study cream was applied to the target tumor and approximately 1 cm (about 1/3 inch) beyond the target tumor prior to normal sleeping hours, and 5 times per week dosing was continued for a total of 6 weeks. The target tumor area was clinically assessed 12 weeks after the last scheduled application of study cream. The entire target tumor was then excised and examined histologically for the presence of tumor.

Efficacy was assessed by the complete response rate defined as the proportion of subjects with clinical (visual) and histological clearance of the sBCC lesion at 12 weeks post-treatment. Of imiquimod-treated subjects, 6% (11/178) who had both clinical and histological assessments post-treatment, and who appeared to be clinically clear had evidence of tumor on excision of the clinically-clear treatment area.

Data on composite clearance (defined as both clinical and histological clearance) are shown in the table below.

Table 12: Composite Clearance Rates at 12 Weeks Post-Treatment
for Superficial Basal Cell Carcinoma
Study | Imiquimod; Cream | Vehicle; Cream
Study; sBCC1 | 70%; (66/94) | 2%; (2/89)
Study; sBCC2 | 80%; (73/91) | 1%; (1/90)
Total | 75%; (139/185) | 2%; (3/179)

A separate 5-year, open-label study was conducted to assess the recurrence of sBCC treated with imiquimod cream applied once daily 5 days per week for 6 weeks. Target tumor inclusion criteria were the same as for the studies described above. At 12-weeks post-treatment, subjects were clinically evaluated for evidence of persistent sBCC (no histological assessment). Subjects with no clinical evidence of sBCC entered the long-term follow-up period. At the 12 week post-treatment assessment, 90% (163/182) of the subjects enrolled had no clinical evidence of sBCC at their target site and 162 subjects entered the long-term follow-up period for up to 5 years. Two year (24 month) follow-up data are available from this study and are presented in the table below:

Table 13: Estimated Clinical Clearance Rates for Superficial Basal Cell Carcinoma
Follow-up Period
Follow-up visit after 12-week post-treatment assessment | No. of Subjects who remained clinically clear | No. of Subjects with sBCC recurrence | No. of Subjects who discontinued at this visit with no sBCCa | Estimated Rate of Subjects who Clinically Cleared and remained Clearb
Month 3 | 153 | 4 | 5 | 87%
Month 6 | 149 | 4 | 0 | 85%
Month 12 | 143 | 2 | 4 | 84%
Month 24 | 139 | 4 | 0 | 79%

a Reasons for discontinuation included death, non-compliance, entry criteria violations, personal reasons, and treatment of nearby sBCC tumor.

b Estimated rate of subjects who clinically cleared and remained clear are estimated based on the time to event analysis employing the life table method beginning with the rate of clinical clearance at 12 weeks post-treatment.

14.3 External Genital Warts

In a double-blind, placebo-controlled clinical study, 209 otherwise healthy subjects 18 years of age and older with genital/perianal warts were treated with imiquimod cream or vehicle control 3 times per week for a maximum of 16 weeks. The median baseline wart area was 69 mm^2 (range 8 to 5525 mm^2). Subject accountability is shown in the figure below.

Data on complete clearance are listed in the table below. The median time to complete wart clearance was 10 weeks.

Table 14: Complete Clearance Rates (External Genital Warts) – Study EGW1

Treatment | Subjects with; Complete; Clearance of Warts | Subjects; Without; Follow-up | Subjects with; Warts Remaining; at Week 16
Overall
Imiquimod Cream (n =109) | 54(50%) | 19(17%) | 36(33%)
Vehicle (n =100) | 11(11%) | 27(27%) | 62(62%)
Females
Imiquimod Cream (n =46) | 33(72%) | 5(11%) | 8(17%)
Vehicle (n =40) | 8(20%) | 13(33%) | 19(48%)
Males
Imiquimod Cream (n =63) | 21(33%) | 14(22%) | 28(44%)
Vehicle (n =60) | 3(5%) | 14(23%) | 43(72%)

16 HOW SUPPLIED/STORAGE AND HANDLING

Imiquimod Cream, 5%, is supplied in single-use packets which contain 250 mg of the cream.

- NDC 72162-2332-2: 24 packets in a Carton

Store at 4-25°C (39-77°F). Avoid freezing.

Keep out of reach of children.

Repackaged/Relabeled by:
Bryant Ranch Prepack, Inc.
Burbank, CA 91504

17 PATIENT COUNSELING INFORMATION

See FDA-Approved Patient Labeling

17.1 General Information: All Indications

Imiquimod Cream should be used as directed by a physician. [see Dosage and Administration (2)] Imiquimod Cream is for external use only. Contact with the eyes, lips and nostrils should be avoided. [see Indications and Usage (1) and Dosage and Administration (2)] The treatment area should not be bandaged or otherwise occluded. Partially-used packets should be discarded and not reused. The prescriber should demonstrate the proper application technique to maximize the benefit of Imiquimod Cream therapy.

It is recommended that patients wash their hands before and after applying Imiquimod Cream.

17.2 Local Skin Reactions: All Indications

Patients may experience local skin reactions during treatment with Imiquimod Cream (even with normal dosing). Potential local skin reactions include erythema, edema, vesicles, erosions/ulcerations, weeping/exudate, flaking/scaling/dryness, and scabbing/crusting. These reactions can range from mild to severe in intensity and may extend beyond the application site onto the surrounding skin. Patients may also experience application site reactions such as itching and/or burning. [see Adverse Reactions (6)]

Local skin reactions may be of such an intensity that patients may require rest periods from treatment. Treatment with Imiquimod Cream can be resumed after the skin reaction has subsided, as determined by the physician. Patients should contact their physician promptly if they experience any sign or symptom at the application site that restricts or prohibits their daily activity or makes continued application of the cream difficult.

Because of local skin reactions, during treatment and until healed, the treatment area is likely to appear noticeably different from normal skin. Localized hypopigmentation and hyperpigmentation have been reported following use of Imiquimod Cream. These skin color changes may be permanent in some patients.

17.3 Systemic Reactions: All Indications

Patients may experience flu-like systemic signs and symptoms during treatment with Imiquimod Cream (even with normal dosing). Systemic signs and symptoms may include malaise, fever, nausea, myalgias and rigors. [see Adverse Reactions (6)] An interruption of dosing should be considered.

17.4 Patients Being Treated for Actinic Keratosis (AK)

Dosing is 2 times per week for a full 16 weeks, unless otherwise directed by the physician. However, the treatment period should not be extended beyond 16 weeks due to missed doses or rest periods. [see Dosage and Administration (2.1)]

It is recommended that the treatment area be washed with mild soap and water 8 hours following Imiquimod Cream application.

Most patients using Imiquimod Cream for the treatment of AK experience erythema, flaking/scaling/dryness and scabbing/crusting at the application site with normal dosing. [see Adverse Reactions (6.1)]

Use of sunscreen is encouraged, and patients should minimize or avoid exposure to natural or artificial sunlight (tanning beds or UVA/B treatment) while using Imiquimod Cream. [see Warnings and Precautions (5.3)]

Sub-clinical AK lesions may become apparent in the treatment area during treatment and may subsequently resolve. [see Clinical Studies (14.1)]

17.5 Patients Being Treated for Superficial Basal Cell Carcinoma (sBCC)

Dosing is 5 times per week for a full 6 weeks, unless otherwise directed by the physician. However, the treatment period should not be extended beyond 6 weeks due to missed doses or rest periods. [see Dosage and Administration (2.2)]

It is recommended that the treatment area be washed with mild soap and water 8 hours following Imiquimod Cream application. [see Dosage and Administration (2.2)]

Most patients using Imiquimod Cream for the treatment of sBCC experience erythema, edema, induration, erosion, scabbing/crusting and flaking/scaling at the application site with normal dosing. [see Adverse Reactions (6.2)]

Use of sunscreen is encouraged, and patients should minimize or avoid exposure to natural or artificial sunlight (tanning beds or UVA/B treatment) while using Imiquimod Cream. [see Warnings and Precautions (5.3)]

The clinical outcome of therapy can be determined after resolution of application site reactions and/or local skin reactions.

Patients with sBCC treated with Imiquimod Cream should have regular follow-up to re-evaluate the treatment site. [see Clinical Studies (14.2)]

17.6 Patients Being Treated for External Genital Warts

Dosing is 3 times per week to external genital/perianal warts. Imiquimod Cream treatment should continue until there is total clearance of the genital/perianal warts or for a maximum of 16 weeks.

It is recommended that the treatment area be washed with mild soap and water 6-10 hours following Imiquimod Cream application.

It is common for patients to experience local skin reactions such as erythema, erosion, excoriation/flaking, and edema at the site of application or surrounding areas. Most skin reactions are mild to moderate.

Sexual (genital, anal, oral) contact should be avoided while Imiquimod Cream is on the skin.

Application of Imiquimod Cream in the vagina is considered internal and should be avoided. Female patients should take special care if applying the cream at the opening of the vagina because local skin reactions on the delicate moist surfaces can result in pain or swelling, and may cause difficulty in passing urine or inability to urinate.

Uncircumcised males treating warts under the foreskin should retract the foreskin and clean the area daily.

New warts may develop during therapy, as Imiquimod Cream is not a cure.

The effect of Imiquimod Cream on the transmission of genital/perianal warts is unknown.

Imiquimod Cream may weaken condoms and vaginal diaphragms, therefore concurrent use is not recommended.

Should severe local skin reaction occur, the cream should be removed by washing the treatment area with mild soap and water.

Rx Only

Made in Israel
Manufactured By Padagis
Yeruham, Israel

Distributed By
Padagis
Allegan, MI 49010 • www.padagis.com
Rev 07-22 2H100 RC J5

Patient Information

IMIQUIMOD CREAM, 5%

Important: For use on the skin only (topical). Do not use Imiquimod Cream in or near your mouth, eyes, nose or vagina.

Read the Patient Information that comes with Imiquimod Cream before you start using it and each time you get a refill. There may be new information. This leaflet does not take the place of talking with your healthcare provider about your medical condition or treatment. If you do not understand the information, or have any questions about Imiquimod Cream, talk with your healthcare provider or pharmacist.

What is Imiquimod Cream?

Imiquimod Cream is a prescription medicine for use on the skin only (topical) to treat:

• actinic keratosis on the face or scalp in adults with a normal immune system. Actinic keratosis is caused by too much sun exposure.

• superficial basal cell carcinoma in adults with a normal immune system when surgery is not recommended.

• Warts on or around the genitals or anus in people 12 years and older.

Imiquimod Cream will not cure your genital or perianal warts. New warts may develop during treatment with Imiquimod Cream. It is not known if Imiquimod Cream can stop you from spreading genital or perianal warts to other people.

It is not known if Imiquimod Cream is safe and effective in:

• people who do not have a normal immune system.

• the treatment of basal cell nevus syndrome.

• the treatment of xeroderma pigmentosum.

• the treatment of actinic keratosis with more than one treatment course in the same affected area.

• the treatment of certain basal cell carcinoma.

It is not known if Imiquimod Cream is safe and effective in children younger than 18 years of age for the treatment of actinic keratosis or superficial basal cell carcinoma. Children usually do not get actinic keratosis or basal cell carcinoma.

It is not known if Imiquimod Cream is safe and effective in children younger than 12 years of age for the treatment of genital and perianal warts.

What should I tell my healthcare provider before using Imiquimod Cream?

Before using Imiquimod Cream, tell your healthcare provider if you:

• have problems with your immune system.

• are being treated or have been treated for actinic keratosis with other medicines or surgery. You should not use Imiquimod Cream until you have healed from other treatments.

• have any other skin problems

• have any other medical conditions

• are pregnant or planning to become pregnant. It is not known if Imiquimod Cream can harm your unborn baby. Talk to your healthcare provider if you are pregnant or plan to become pregnant.

• are breastfeeding or plan to breastfeed. It is not known if Imiquimod Cream passes into your breast milk and if it can harm your baby. Talk to your healthcare provider about the best way to feed your baby if you use Imiquimod Cream.

Tell your healthcare provider about all the medicines you take, including prescription and non-prescription medicines, vitamins and herbal supplements.

Especially tell your healthcare provider if you have had other treatments for genital warts or warts around your anus, or actinic keratosis, or superficial basal cell carcinoma. Imiquimod Cream should not be used until your skin has healed from other treatments. Know the medicines you take. Keep a list of them to show your healthcare provider and pharmacist when you get a new medicine.

How should I use Imiquimod Cream?

• Do not get Imiquimod Cream in or near your mouth, eyes, nose or vagina.

• Use Imiquimod Cream exactly as your healthcare provider tells you to use it. Your healthcare provider will tell you where to apply Imiquimod Cream and how often and for how long to apply it for your condition.

• Imiquimod Cream is used for different skin conditions. Use Imiquimod Cream only on the area of your body to be treated. Do not apply Imiquimod Cream to other areas.

• Do not use Imiquimod Cream longer than prescribed. Using too much Imiquimod Cream, or using it too often, or for too long can increase your chances for having a severe skin reaction or other side effect.

• You should follow-up with your healthcare provider regularly for check-ups while using Imiquimod Cream.

• Talk to your healthcare provider if you think Imiquimod Cream is not working for you.

Applying Imiquimod Cream

Imiquimod Cream should be applied just before your bedtime.

• Wash the area where the cream will be applied with mild soap and water. Uncircumcised males treating warts under their penis foreskin must pull their foreskin back and clean the area before treatment, and clean the area daily during treatment.

• Allow the area to dry for at least 10 minutes.

• Wash your hands.

• Open a new packet of Imiquimod Cream.

• Apply a thin layer of Imiquimod Cream only to the affected area. Do not use more Imiquimod Cream than is needed to cover the affected area.

• Rub the cream into your skin until you can not see the Imiquimod Cream. After applying Imiquimod Cream, wash your hands well.

• Leave the cream on the treated area for the amount of time your healthcare provider tells you. The length of time that Imiquimod Cream is left on the skin is different for each skin condition that Imiquimod Cream is used to treat. Do not take a bath or get the treated area wet during this time.

• After the right amount of time has passed, wash the treated area with mild soap and water.

• If you get Imiquimod Cream in your mouth or in your eyes, rinse well with water right away.

What should I avoid while using Imiquimod Cream?

• Do not cover the treated area with bandages or other closed dressings.

• Do not use sunlamps or tanning beds, and avoid sunlight as much as possible during treatment with Imiquimod Cream. Use sunscreen and wear protective clothing if you go outside during daylight.

• Do not have sexual contact including genital, anal, or oral sex when Imiquimod Cream is on your genitals or the skin around your anus. Imiquimod Cream may weaken condoms and vaginal diaphragms. This means they may not work as well to prevent pregnancy.

What are the possible side effects of Imiquimod Cream?

Imiquimod Cream may cause serious side effects including:

Local skin reactions, including:

• skin drainage (weeping)

• ulcers

• severe swelling near the vagina. This may lead to pain or trouble passing urine or cause you not to be able to urinate. Female patients should take special care when applying Imiquimod Cream at the opening of the vagina.

Flu-like symptoms: tiredness, fever, nausea, muscle pain and chills.

Tell your healthcare provider right away if you have any of the symptoms listed above.

The most common side effects of Imiquimod Cream include:

• itching

• burning

• redness

• flaking and scaling

• dryness

• scabbing and crusting

• swelling

• skin that becomes hard or thickened

• sores, blisters, or ulcers

• changes in skin color that do not always go away

Tell your healthcare provider if you have any side effect that bothers you or that does not go away.

These are not all the side effects of Imiquimod Cream. For more information, ask your healthcare provider or pharmacist.

Call your doctor for medical advice about side effects. You may report side effects to Padagis at 1-866-634-9120 or FDA at 1-800-FDA-1088 or www.fda.gov/medwatch.

How do I store Imiquimod Cream?

• Store Imiquimod Cream between 39ºF to 77°F (4ºC to 25ºC).

• Do not freeze.

• Safely throw away unused Imiquimod Cream or partially used Imiquimod Cream packets that you do not need.

Keep Imiquimod Cream and all medicines out of the reach of children.

General information about the safe and effective use of Imiquimod Cream

Medicines are sometimes prescribed for purposes other than those listed in this Patient Information leaflet. Do not use Imiquimod Cream for a condition for which it was not prescribed. Do not give Imiquimod Cream to other people, even if they have the same symptoms you have. It may harm them.

This Patient Information leaflet summarizes the most important information about Imiquimod Cream. If you would like more information, talk with your healthcare provider. You can ask your pharmacist or healthcare provider for information about Imiquimod Cream that is written for the healthcare professionals.

What are the ingredients in Imiquimod Cream?

Active Ingredient: imiquimod

Inactive ingredients: benzyl alcohol, cetyl alcohol, glycerin, methylparaben, oleic acid, oleyl alcohol, polysorbate 60, propylparaben, purified water, stearyl alcohol, sorbitan monostearate, white petrolatum, and xanthan gum.

Made in Israel

Manufactured By Padagis
Yeruham, Israel

Distributed By
Padagis
Allegan, MI 49010 • www.padagis.com

Rev 07-22

PACKAGE LABEL

Imiquimod 5% Cream